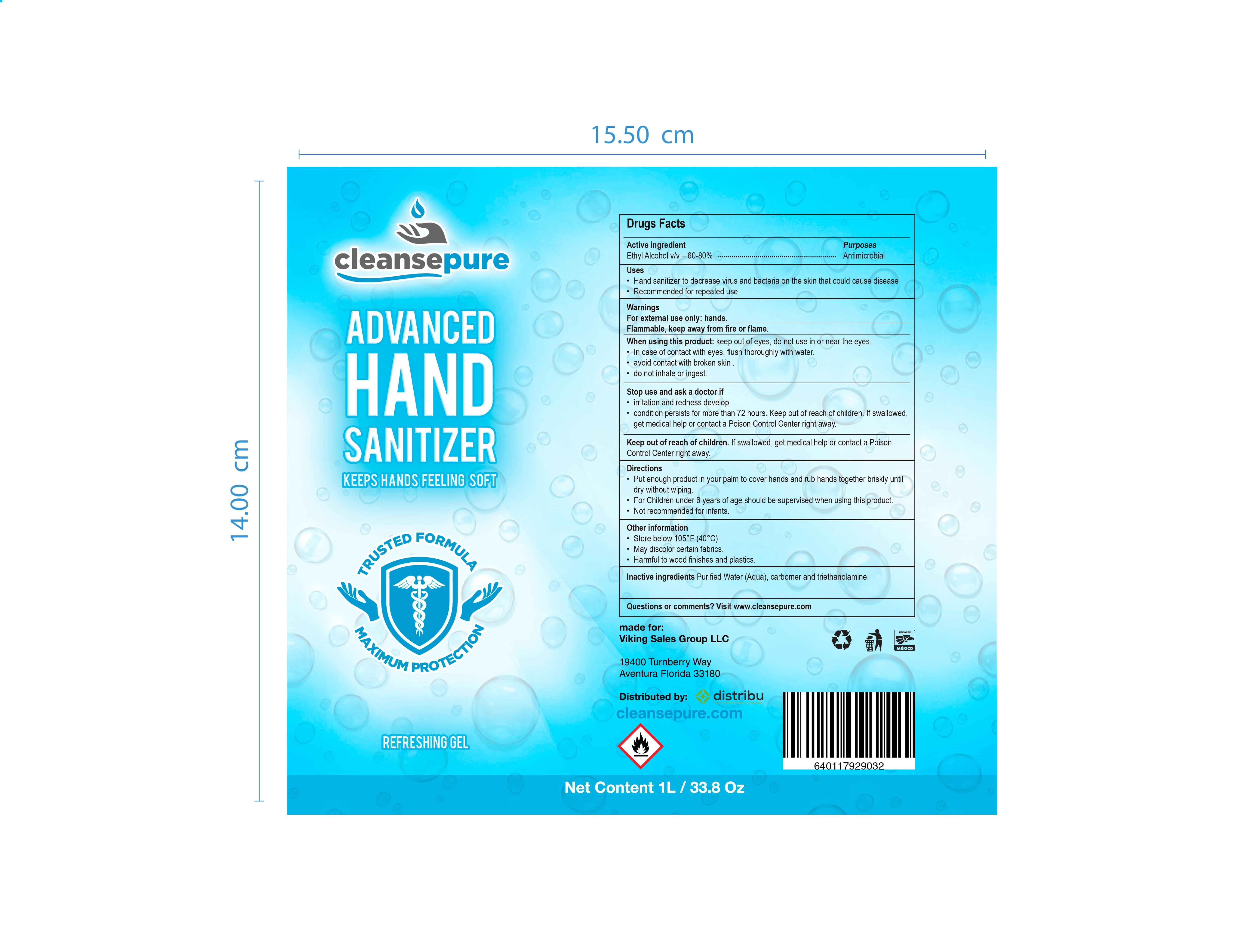 DRUG LABEL: HAND SANITIZER
NDC: 74543-193 | Form: GEL
Manufacturer: MARGREY INDUSTRIAL SA DE CV
Category: otc | Type: HUMAN OTC DRUG LABEL
Date: 20200611

ACTIVE INGREDIENTS: ALCOHOL 70 mL/100 mL
INACTIVE INGREDIENTS: CARBOXYMETHYLCELLULOSE 0.1 mL/100 mL; WATER 29.6 mL/100 mL; HYPROMELLOSE 2208 (60000 MPA.S) 0.1 mL/100 mL; GLYCERIN 0.2 mL/100 mL; CARBOMER HOMOPOLYMER TYPE C (ALLYL PENTAERYTHRITOL CROSSLINKED) 0.4 mL/100 mL

Active ingredient

Ethyl Alcohol v/v 60-80%

Purposes

Antimicrobial

Uses

Hand sanitizer to decrease virus and bacteria on the skin that could cause disease

Recommended for repetead use

Warnings

For external use only: hands

Flammable, keep away from fire and flame

When using this product

keep out of eyes, do not use in or near the eyes

In case of contact with eyes, flush thorougly with water

Avoid contact with broken skin

Do not inhale or ingest

When using this product

keep out of eyes, do not use in or near the eyes

In case of contact with eyes, flush thorougly with water

Avoid contact with broken skin

Do not inhale or ingest

Stop use and ask a doctor if

irritation and redness develop

condition persists for more than 72 hours. Keep out of reach of children. If swallowed, get medical help or contact a poison control center right away

keep out of reach of children

if swallowed, get medical help or contact a poison control center right away

Directions

Put enough product in your palm to cover hands and rub hands together briskly until dry without wiping

For children under 6 years of age should be supervised when using this product

not recommended for infants

other information

store below 105 f 40 c

may discolor certain fabrics

harmful to wood finishes and plastics

inactive ingredients

purified water, hydroxypropyl methylcellulose hpmc, carboxymethyl cellulose, carbomer, glycerine usp

questions or comments

visit www.cleanspure.com

PRINCIPAL DISPLAY

ADVANCED HAND SANITIZER

KEEP HANDS FEELING SOFT

TRUSTED FORMULA

MAZIMUN PROTECTION

REFRESHING GEL